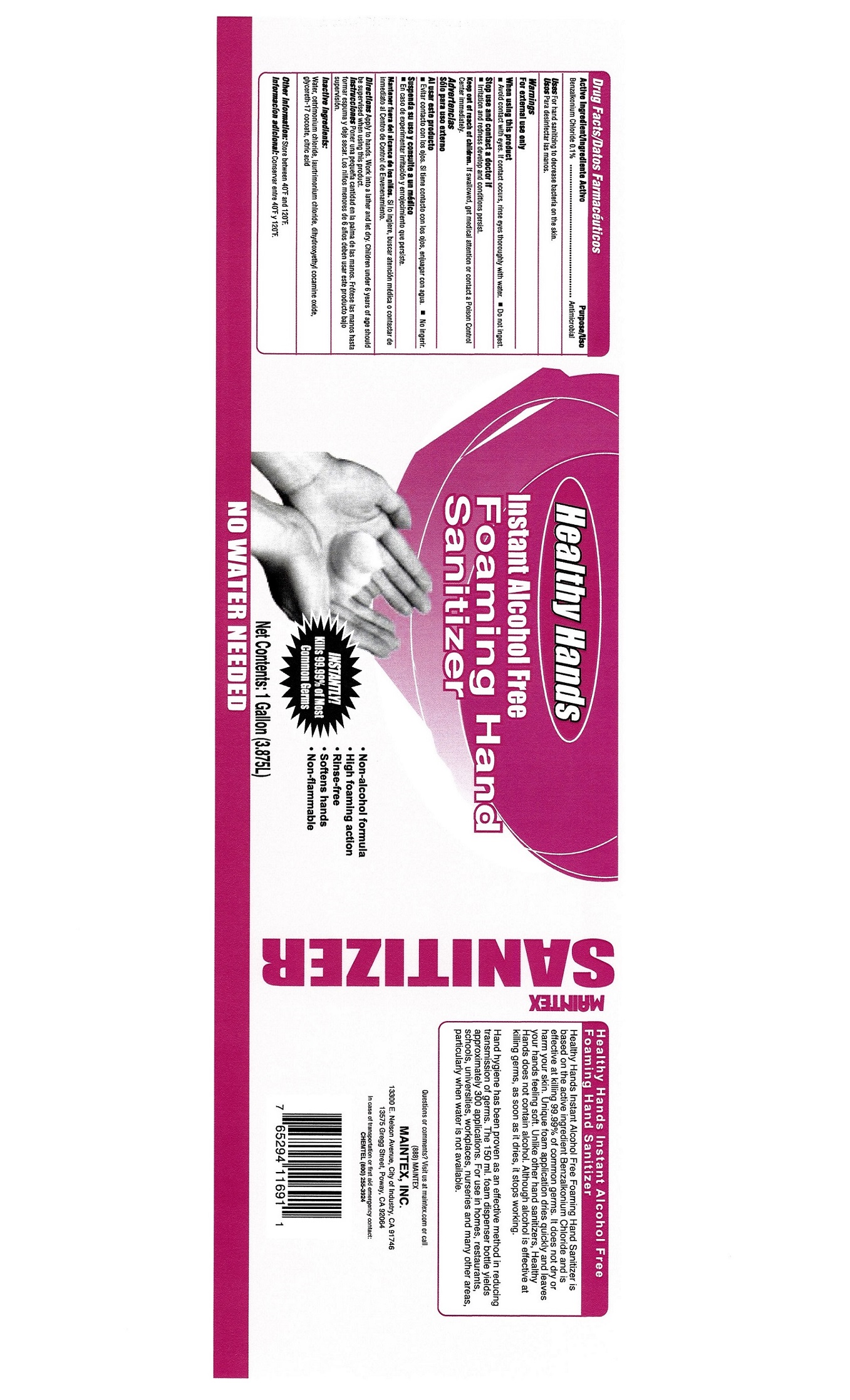 DRUG LABEL: Healthy  Hands Foaming Hand Sanitizer
NDC: 77617-001 | Form: LIQUID
Manufacturer: Maintex
Category: otc | Type: HUMAN OTC DRUG LABEL
Date: 20251222

ACTIVE INGREDIENTS: BENZALKONIUM CHLORIDE 0.1 g/100 g
INACTIVE INGREDIENTS: WATER; CETRIMONIUM CHLORIDE; LAURTRIMONIUM CHLORIDE; DIHYDROXYETHYL COCAMINE OXIDE; GLYCERETH-17 COCOATE; CITRIC ACID MONOHYDRATE

Healthy Hands Foaming Hand Sanitizer

Active Ingredient

Benzalkonium Chloride...........................0.1 %

Uses

- For hand sanitizing to decrease bacteria on the skin

Purpose

Antimicrobial

Warnings

- For external use only
- When using this product avoid contact with eyes. If contact occurs, rinse eyes thoroughly with water. Do not ingest.
- Stop use and ask a doctor if irritation and redness develop and conditions persist.

Keep out of reach of children. If swallowed, get medical attention or contact a Poison Conrol Center immediately.

Directions

- Apply to hands. Work into a lather and let dry.
- Children under 6 years of age should be supervised when using this product.

Inert Ingredients:

Inactive Ingredients

- water
- cetrimonium chloride
- laurtrimonium chloride
- dihydroxyethyl cocamine oxide
- glycereth-17 cocoate
- citric acid